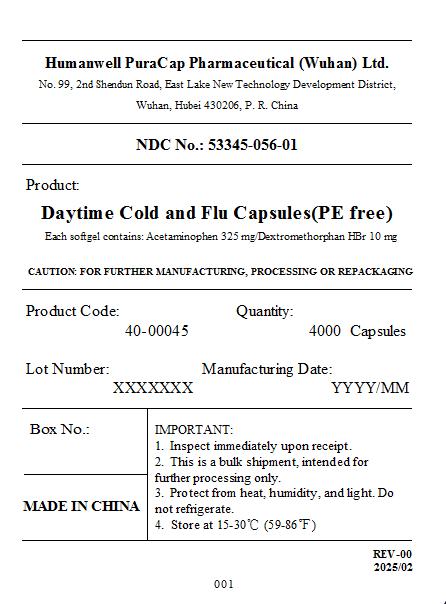 DRUG LABEL: Daytime Cold and Flu
NDC: 53345-056 | Form: CAPSULE, LIQUID FILLED
Manufacturer: Humanwell PuraCap Pharmaceuticals (Wuhan) Co., Ltd
Category: otc | Type: HUMAN OTC DRUG LABEL
Date: 20251223

ACTIVE INGREDIENTS: DEXTROMETHORPHAN HYDROBROMIDE 10 mg/1 1; ACETAMINOPHEN 325 mg/1 1
INACTIVE INGREDIENTS: GLYCERIN; GELATIN TYPE B BOVINE (150 BLOOM); POLYETHYLENE GLYCOL 400; WATER; SORBITOL; POVIDONE K12; SORBITAN; PROPYLENE GLYCOL; FD&C RED NO. 40; FD&C YELLOW NO. 6

Daytime Cold and Flu Capsules (PE free)

Drug Facts

Active Ingredients (in each softgel)

Acetaminophen 325 mg

Dextromethorphan HBr 10 mg

Purpose

Pain Reliever/Fever Reducer

Cough Suppressant

Uses

Temporarily relieves common cold/flu symptoms:

- cough due to minor throat and bronchial irritation
- sore throat
- headache
- minor aches and pains
- fever

Warnings

Liver warning

This product contains acetaminophen. Severe liver damage may occur if you take

- more than 4 doses in 24 hours, which is the maximum daily amount for this product
- with other drugs containing acetaminophen
- 3 or more alcoholic drinks every day while using this product

Allergy alert

Acetaminophen may cause severe skin reactions. Symptoms may include:

- skin reddening
- blisters
- rash

If a skin reaction occurs, stop use and seek medical help right away

Sore throat warning

If sore throat is severe, lasts for more than 2 days, is accompanied or followed by fever, headache, rash, nausea, or vomiting, consult a doctor promptly.

Do not use

- with any other drug containing acetaminophen (prescription or nonprescription). If you are not sure whether a drug contains acetaminophen, ask a doctor or pharmacist.
- if you are now taking a prescription monoamine oxidase inhibitor (MAOI) (certain drugs for depression, psychiatric, or emotional conditions, or Parkinson's disease), or for 2 weeks after stopping the MAOI drug. If you do not know if your prescription drug contains an MAOI, ask a doctor or pharmacist before taking this product.
- if you have ever had an allergic reaction to this product or any of its ingredients

Ask a doctor before use if you have

- liver disease
- cough that occurs with too much phlegm (mucus)
- persistent or chronic cough as occurs with smoking, asthma, or emphysema

When using this product do not exceed recommended dose.

Stop use and ask a doctor if

- pain or cough gets worse or lasts more than 5 days (children) or 7 days (adults)
- fever gets worse or lasts more than 3 days
- redness or swelling is present
- new symptoms occur
- cough comes back or occurs with rash or headache that lasts.

These could be signs of a serious condition.

PREGNANCY OR BREAST FEEDING

If pregnant or breast-feeding, ask a health professional before use.

Keep out of reach of children.

Overdose warning

In case of accidental overdose, seek professional assistance or contact a Poison Control Center immediately.

Prompt medical attention is critical for adults as well as for children even if you do not notice any signs or symptoms.

Directions

- Take only as directed (see overdose warning)
- Do not take more than 4 doses in 24 hours.

adults and children 12 years and over | 2 softgels with water every 4 hours
children 4 to under 12 years | consult a doctor
children under 4 years | do not use

Other information

- Store at 15° - 30 °C (59°- 86 °F)
- Read all product information before using.
- Tamper evident: Do not use if carton is open or blister unit is broken.

Inactive ingredients

FD&C Red # 40, FD&C Yellow # 6, Gelatin, Glycerin, Polyethylene Glycol 400, Povidone K12, Propylene Glycol, Purified water, Sorbitol Sorbitan Solution, White ink.

QUESTIONS OR COMMENTS?

Call toll free: 1-855-215-8180

PRINCIPAL DISPLAY PANEL

Daytime Cold and Flu Capsules (PE free)

Each softgel contains: Acetaminophen 325mg/ Dextromethorphan HBr 10mg

NDC 53345-056-01

Caution: for further manufacturing, processing or repackaing